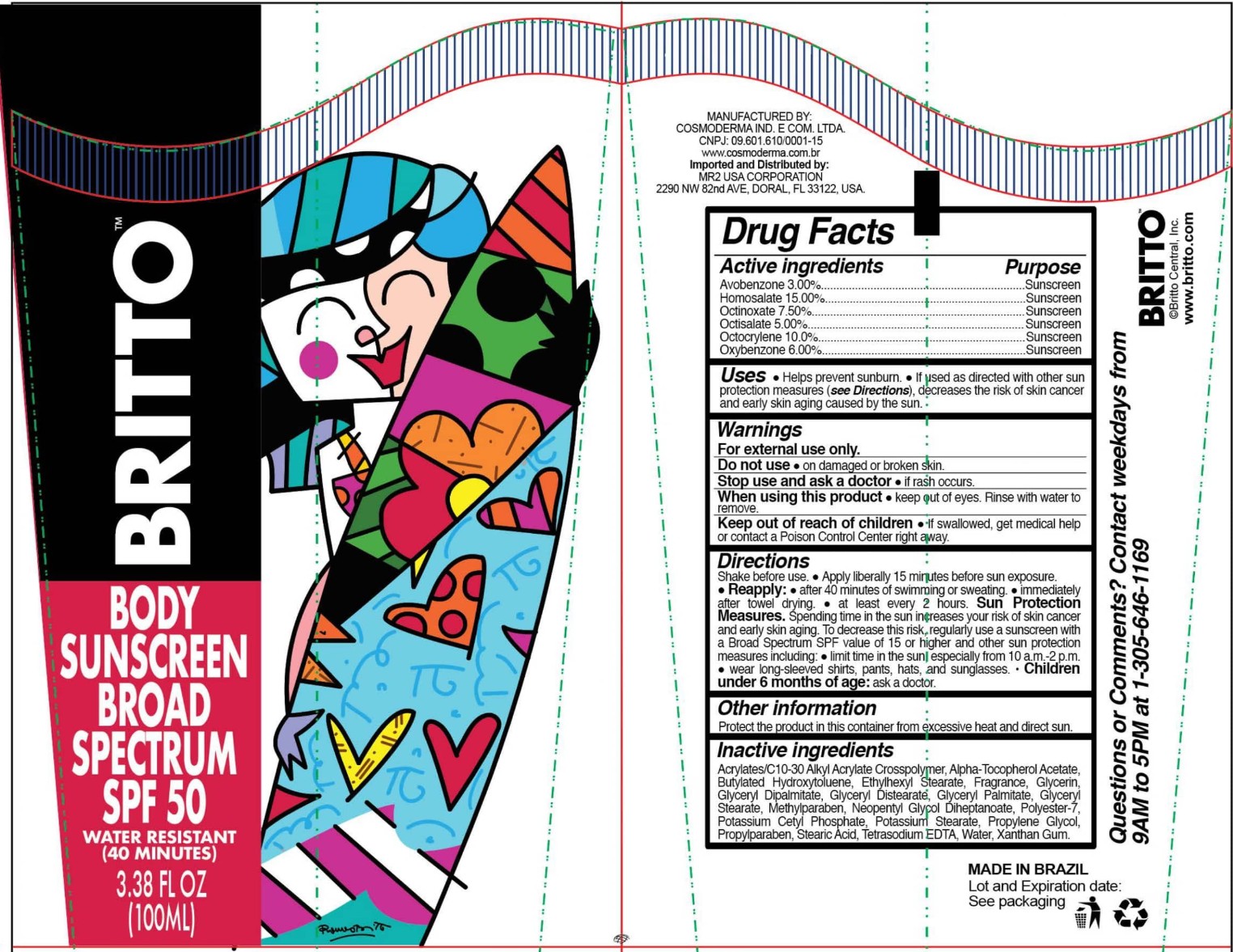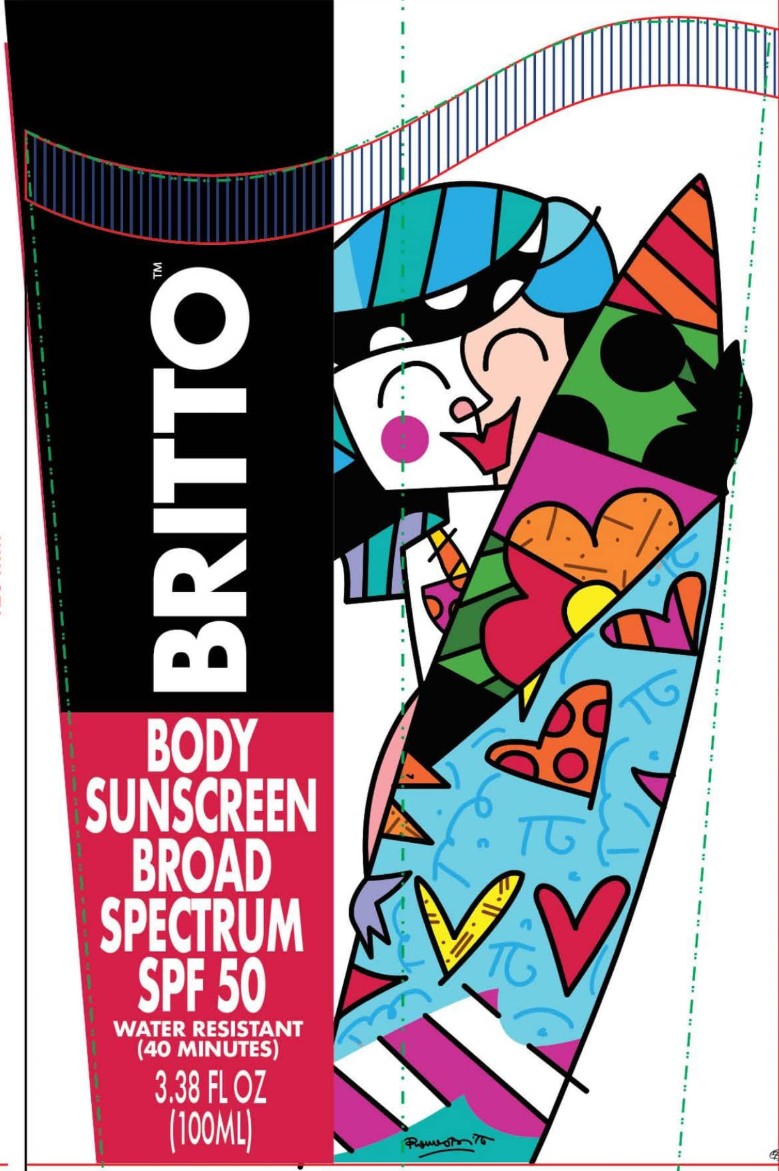 DRUG LABEL: Britto Body Sunscreen Broad Spectrum SPF 50
NDC: 77069-002 | Form: CREAM
Manufacturer: MR2 USA Corporation
Category: otc | Type: HUMAN OTC DRUG LABEL
Date: 20201227

ACTIVE INGREDIENTS: OCTOCRYLENE 10 g/100 mL; OCTISALATE 5 g/100 mL; AVOBENZONE 3 g/100 mL; OXYBENZONE 6 g/100 mL; HOMOSALATE 15 g/100 mL; OCTINOXATE 7.5 g/100 mL
INACTIVE INGREDIENTS: GLYCERYL PALMITATE 1.32 g/100 mL; WATER 37.05 g/100 mL; GLYCERYL MONOSTEARATE 2.24 g/100 mL; PROPYLENE GLYCOL 2 g/100 mL; GLYCERYL DIPALMITATE 1.32 g/100 mL; XANTHAN GUM 0.2 g/100 mL; POLYESTER-7 0.6 g/100 mL; STEARIC ACID 0.6 g/100 mL; CARBOMER COPOLYMER TYPE B (ALLYL PENTAERYTHRITOL CROSSLINKED) 0.2 g/100 mL; ALPHA-TOCOPHEROL ACETATE 0.5 g/100 mL; METHYLPARABEN 0.2 g/100 mL; GLYCERYL DISTEARATE 1.84 g/100 mL; ETHYLHEXYL STEARATE 3 g/100 mL; POTASSIUM CETYL PHOSPHATE 1 g/100 mL; NEOPENTYL GLYCOL DIHEPTANOATE 0.4 g/100 mL; POTASSIUM STEARATE 0.36 g/100 mL; GLYCERIN 0.32 g/100 mL; BUTYLATED HYDROXYTOLUENE 0.1 g/100 mL; PROPYLPARABEN 0.1 g/100 mL; EDETATE SODIUM 0.05 g/100 mL

NO CHANGE NOTIFICATION